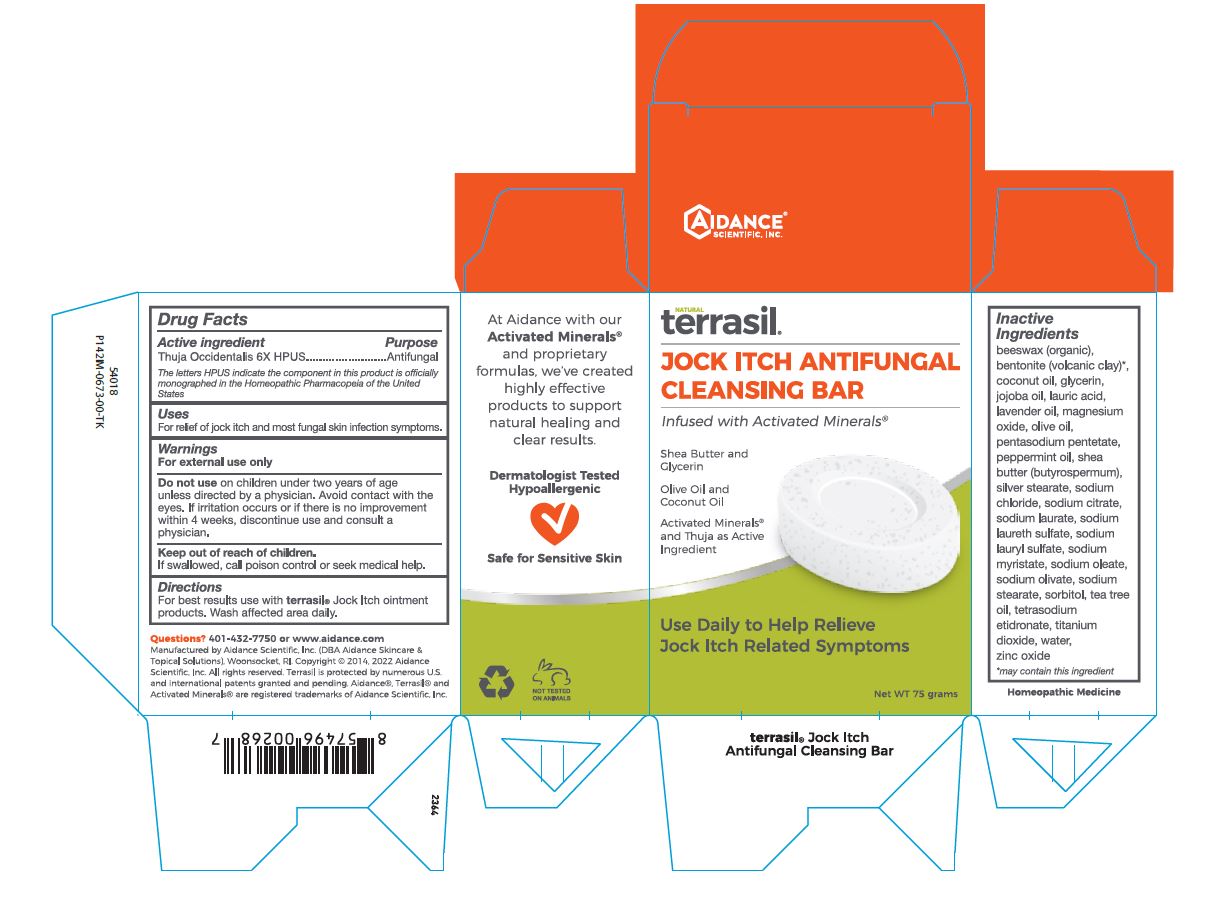 DRUG LABEL: terrasil Jock Itch Antifungal Cleansing Bar
NDC: 24909-045 | Form: SOAP
Manufacturer: Aidance Scientific, Inc., DBA Aidance Skincare & Topical Solutions
Category: homeopathic | Type: HUMAN OTC DRUG LABEL
Date: 20241122

ACTIVE INGREDIENTS: THUJA OCCIDENTALIS WHOLE 6 [hp_X]/1 g
INACTIVE INGREDIENTS: JOJOBA OIL; SODIUM STEARATE; SORBITOL; LAURIC ACID; SODIUM CHLORIDE; YELLOW WAX; LAVENDER OIL; PENTASODIUM PENTETATE; PEPPERMINT OIL; SODIUM LAURETH SULFATE; SODIUM OLIVATE; TITANIUM DIOXIDE; COCONUT OIL; SILVER STEARATE; ZINC OXIDE; GLYCERIN; MAGNESIUM OXIDE; SODIUM LAURATE; OLIVE OIL; SODIUM CITRATE; SODIUM OLEATE; ETIDRONATE TETRASODIUM; SHEA BUTTER; WATER; SODIUM LAURYL SULFATE; SODIUM MYRISTATE; TEA TREE OIL

24909-045 terrasil Jock Itch Cleansing Bar

Active ingredient

Thuja Occidentalis 6X HPUS - Antifungal

The letters HPUS indicate the component in this product is officialy monographed in the Homeopathic Pharmacopeia of the United States.

Purpose

For relief of jock itch and most fungal skin infection symptoms.

Uses

For relief of jock itch and most fungal skin infection symptoms.

Warnings

For external use only.

Do not use on children under two years of age unless directed by a physician. Avoid contact with the eyes. If irritation occurs or if there is no improvement within 4 weeks, discontinue use and consult a physician.

Keep out of reach of children.

OTHER SAFETY INFORMATION

If swalowed, cal poison control or seek medical help.

Directions

For best results use with terrasil® Jock Itch ointment products. Wash affected area daily.

Inactive ingredients

beeswax (organic), bentonite (volcanic clay)*, coconut oil, glycerin, jojoba oil, lauric acid, lavender oil, magnesium oxide, olive oil, pentasodium pentetate, peppermint oil, shea butter (butyrospermum), silver stearate, sodium chloride, sodium citrate, sodium laurate, sodium laureth sulfate, sodium lauryl sulfate, sodium myristate, sodium oleate, sodium olivate, sodium stearate, sorbitol, tea tree oil, tetrasodium etidronate, titanium dioxide, water, zinc oxide *may contain this ingredient

Questions? 401-432-7750 or www.aidance.com